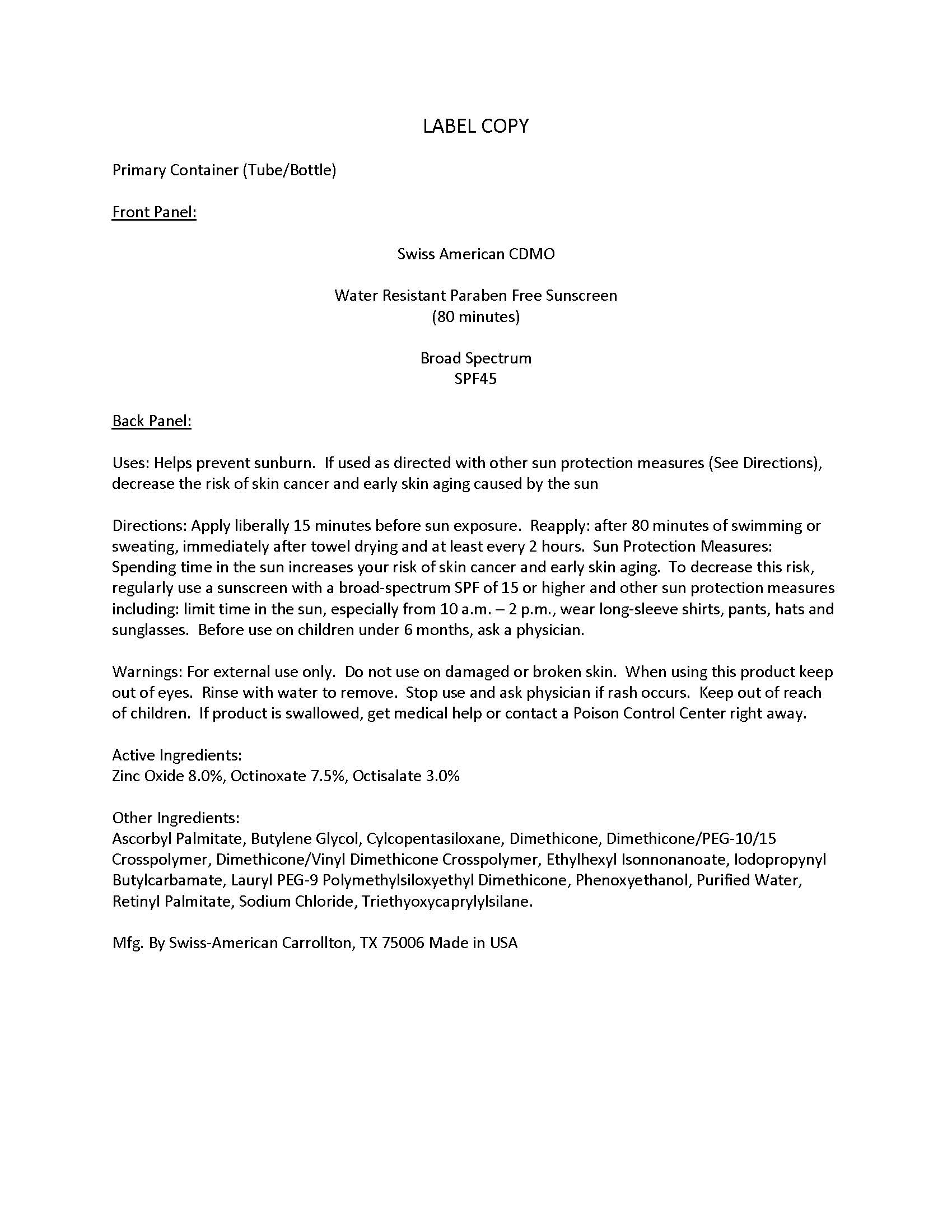 DRUG LABEL: Private Label SPF45 Water Resistant Paraben Free Sunscreen
NDC: 60232-0006 | Form: LOTION
Manufacturer: Swiss-American CDMO, LLC
Category: otc | Type: HUMAN OTC DRUG LABEL
Date: 20231107

ACTIVE INGREDIENTS: ZINC OXIDE 80 g/1000 g; OCTINOXATE 75 g/1000 g; OCTISALATE 30 g/1000 g
INACTIVE INGREDIENTS: VITAMIN A PALMITATE; DIMETHICONE/VINYL DIMETHICONE CROSSPOLYMER (SOFT PARTICLE); LAURYL PEG-9 POLYDIMETHYLSILOXYETHYL DIMETHICONE; ETHYLHEXYL ISONONANOATE; TRIETHOXYCAPRYLYLSILANE; BUTYLENE GLYCOL; PHENOXYETHANOL; IODOPROPYNYL BUTYLCARBAMATE; WATER; SODIUM CHLORIDE; CYCLOMETHICONE 5; ASCORBYL PALMITATE

Private Label SPF45 Water Resistant Paraben Free Sunscreen

Warnings

For external use only. Do not use on damaged or broken skin. When using this product keep out of eyes. Rinse with water to remove. Stop use and ask physician if rash occurs. Keep out of reach of children. If product is swallowed, get medical help or contact a Poison Control Center right away.

Uses

Helps prevent sunburn. If used as directed with other sun protection measures (See Directions), decrease the risk of skin cancer and early skin aging caused by the sun

Uses

Helps prevent sunburn. If used as directed with other sun protection measures (See Directions), decrease the risk of skin cancer and early skin aging caused by the sun

Directions

Apply liberally 15 minutes before sun exposure. Reapply: after 80 minutes of swimming or sweating, immediately after towel drying and at least every 2 hours. Sun Protection Measures: Spending time in the sun increases your risk of skin cancer and early skin aging. To decrease this risk, regularly use a sunscreen with a broad-spectrum SPF of 15 or higher and other sun protection measures including: limit time in the sun, especially from 10 a.m. – 2 p.m., wear long-sleeve shirts, pants, hats and sunglasses. Before use on children under 6 months, ask a physician.

Keep Out of Reach of Children

Active Ingredients

Zinc Oxide 8.0%, Octinoxate 7.5%, Octisalate 3.0%

Inactive Ingredients

Ascorbyl Palmitate, Butylene Glycol, Cylcopentasiloxane, Dimethicone, Dimethicone/PEG-10/15 Crosspolymer, Dimethicone/Vinyl Dimethicone Crosspolymer, Ethylhexyl Isonnonanoate, Iodopropynyl Butylcarbamate, Lauryl PEG-9 Polymethylsiloxyethyl Dimethicone, Phenoxyethanol, Purified Water, Retinyl Palmitate, Sodium Chloride, Triethyoxycaprylylsilane